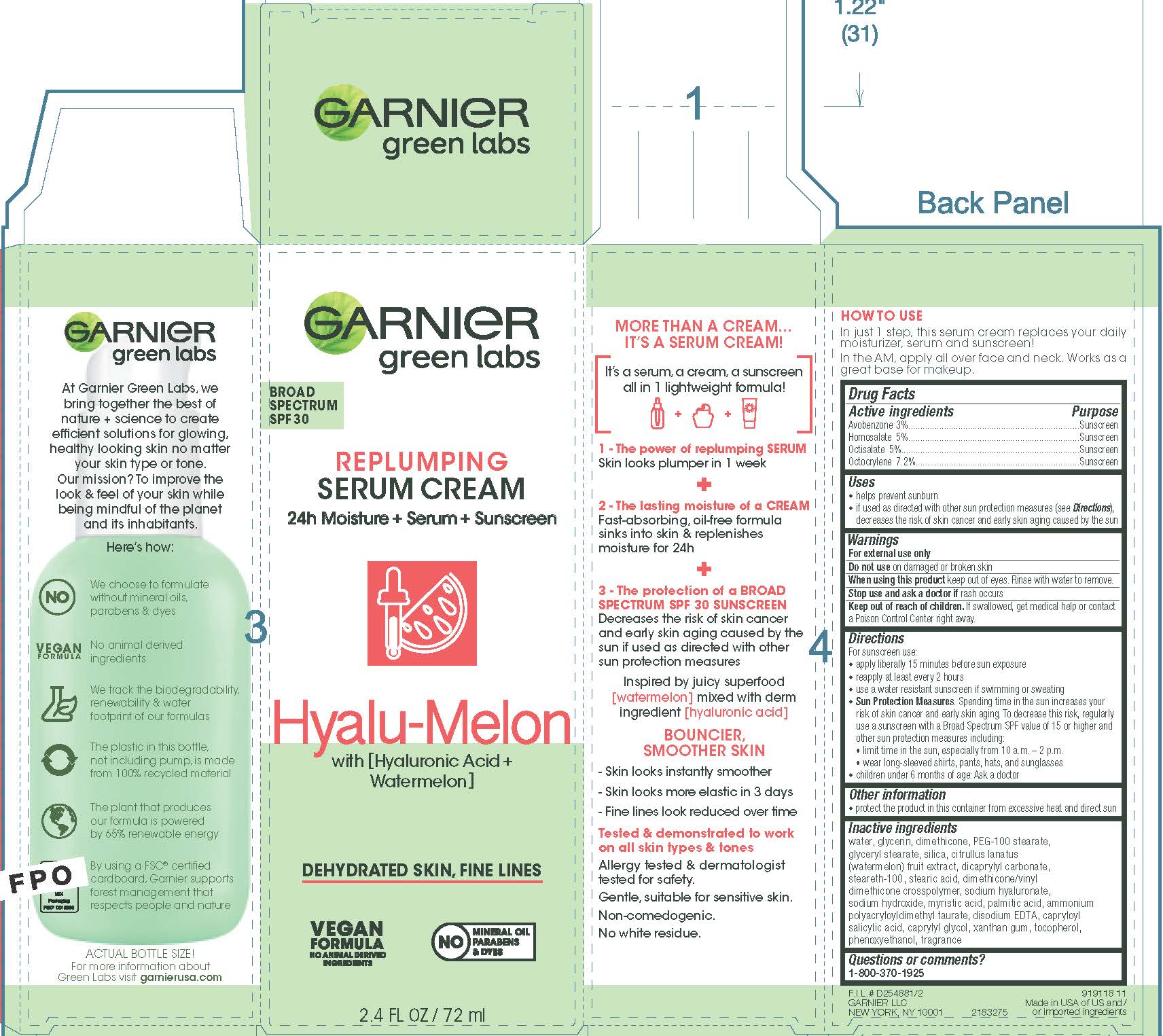 DRUG LABEL: Garnier green labs Replumping HyaluMelon Broad Spectrum SPF 30 Sunscreen
NDC: 49967-290 | Form: CREAM
Manufacturer: L’Oreal USA Products Inc
Category: otc | Type: HUMAN OTC DRUG LABEL
Date: 20240102

ACTIVE INGREDIENTS: AVOBENZONE 30 mg/1 mL; HOMOSALATE 50 mg/1 mL; OCTISALATE 50 mg/1 mL; OCTOCRYLENE 72 mg/1 mL
INACTIVE INGREDIENTS: WATER; GLYCERIN; DIMETHICONE; PEG-100 STEARATE; GLYCERYL MONOSTEARATE; SILICON DIOXIDE; WATERMELON; DICAPRYLYL CARBONATE; STEARETH-100; STEARIC ACID; DIMETHICONE/VINYL DIMETHICONE CROSSPOLYMER (SOFT PARTICLE); HYALURONATE SODIUM; SODIUM HYDROXIDE; MYRISTIC ACID; PALMITIC ACID; AMMONIUM POLYACRYLOYLDIMETHYL TAURATE (55000 MPA.S); EDETATE DISODIUM; CAPRYLOYL SALICYLIC ACID; CAPRYLYL GLYCOL; XANTHAN GUM; TOCOPHEROL; PHENOXYETHANOL

Drug Facts

Active ingredient

Avobenzone 3%

Homosalate 5%

Octisalate 5%

Octocrylene 7.2%

Purpose

Sunscreen

Uses

- helps prevent sunburn
- if used as directed with other sun protection measures (see Directions), decreases the risk of skin cancer and early skin aging caused by the sun

Warnings

For external use only

Do not use

on damaged or broken skin

When using this product

keep out of eyes. Rinse with water to remove.

Stop use and ask a doctor if

rash occurs

Keep out of reach of children.

If swallowed, get medical help or contact a Poison Control Center right away.

Directions

For sunscreen use:

- apply liberally 15 minutes before sun exposure
- reapply at least every 2 hours
- use a water resistant sunscreen if swimming or sweating
- Sun Protection Measures. Spending time in the sun increases your risk of skin cancer and early skin aging. To decrease this risk, regularly use a sunscreen with a Broad Spectrum SPF value of 15 or higher and other sun protection measures including:

● limit time in the sun, especially from 10 a.m. – 2 p.m.

● wear long-sleeved shirts, pants, hats, and sunglasses

- children under 6 months of age: Ask a doctor

Other information

protect the product in this container from excessive heat and direct sun

Inactive ingredients

water, glycerin, dimethicone, PEG-100 stearate, glyceryl stearate, silica, citrullus lanatus (watermelon) fruit extract, dicaprylyl carbonate, steareth-100, stearic acid, dimethicone/vinyl dimethicone crosspolymer, sodium hyaluronate, sodium hydroxide, myristic acid, palmitic acid, ammonium polyacryloyldimethyl taurate, disodium EDTA, capryloyl salicylic acid, caprylyl glycol, xanthan gum, tocopherol, phenoxyethanol, fragrance

Questions or comments?

1-800-370-1925